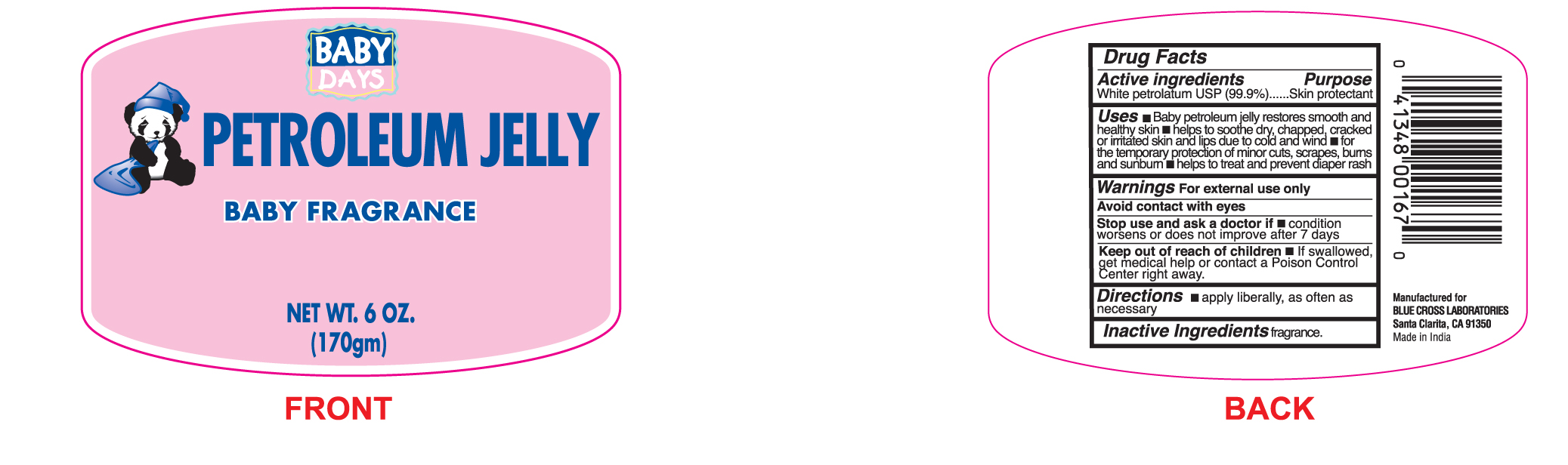 DRUG LABEL: Petroleum Jelly Baby Fragrance
NDC: 22431-134 | Form: JELLY
Manufacturer: Blue Cross Laboratories, Inc.
Category: otc | Type: HUMAN OTC DRUG LABEL
Date: 20201113

ACTIVE INGREDIENTS: PETROLATUM 99.9 1/100 g

Baby Days Petroleum Jelly Baby Fragrance

Active ingredients Purpose

White Petrolatum USP(100%) Skin Protectant

Uses

- Baby Petroleum Jelly Restores smooth and healthy skin
- Helps to soothe dry, chapped, cracked, or irritated skin and lips due to cold and wind
- for the temporary protection of minor cuts, scrapes, burns and sunburn
- helps to treat and prevent diaper rash

Keep out of reach of children.

If swallowed, get medical help or contact a Poison Control Center right away.

Stop use and ask a doctor if condition worsens or does not improve after 7 days

Warnings

For external use only

Avoid Contact with eyes

Directions

apply liberally, as often as necessary

Inactive Ingredients fragrance

PACKAGE LABEL

Baby Days

Petroleum Jelly Baby Fragrance

Net Wt. 6 oz.